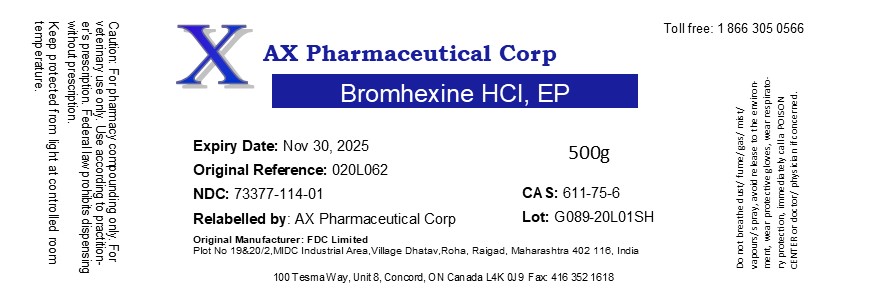 DRUG LABEL: Bromhexine HCl
NDC: 73377-114 | Form: POWDER
Manufacturer: AX Pharmaceutical Corp
Category: other | Type: BULK INGREDIENT
Date: 20210223

ACTIVE INGREDIENTS: BROMHEXINE HYDROCHLORIDE 1 g/1 g

Bromhexine HCl